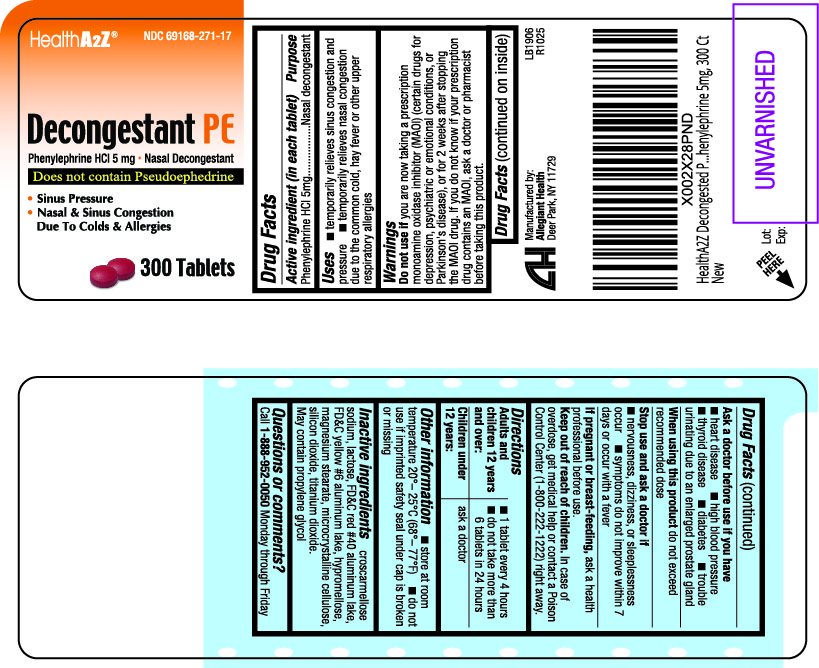 DRUG LABEL: Decongestant PE
NDC: 69168-271 | Form: TABLET
Manufacturer: Allegiant Health
Category: otc | Type: HUMAN OTC DRUG LABEL
Date: 20210616

ACTIVE INGREDIENTS: PHENYLEPHRINE HYDROCHLORIDE 5 mg/1 1
INACTIVE INGREDIENTS: CROSCARMELLOSE SODIUM; LACTOSE, UNSPECIFIED FORM; FD&C RED NO. 40; FD&C YELLOW NO. 6; HYPROMELLOSES; MAGNESIUM STEARATE; MICROCRYSTALLINE CELLULOSE; SILICON DIOXIDE; TITANIUM DIOXIDE

271 - Phenylephrine HCL 5mg

Active ingredient(s)

Phenylephrine HCl 5mg

Purpose

Nasal decongestant

Use(s)

- temporarily relieves sinus congestion and
  pressure
- temporarily relieves nasal congestion due to the
  common cold, hay fever or other upper respiratory
  allergies

Warnings

you are now taking a prescription monoamine
oxidase inhibitor (MAOI) (certain drugs for
depression, psychiatric or emotional conditions, or
Parkinson's disease), or for 2 weeks after stopping the
MAOI drug. If you do not know if your prescription drug
contains an MAOI, ask a doctor or pharmacist before
taking this product.

Ask a doctor before use if

- heart disease
- high blood pressure
- thyroid disease
- diabetes
- trouble urinating due to an enlarged prostate gland

When using this product

do not exceed recommended dose

Stop use and ask a doctor if

- nervousness, dizziness, or sleeplessness occur
- symptoms do not improve within 7 days or occur with a fever

Pregnancy/Breastfeeding

ask a health professional before use

Keep out of reach of children

In case of overdose, get medical help or contact a Poison Control Center (1-800-222-1222) right away.

Directions

Adults and children 12 years and over: 1 tablet every 4 hours

- do not take more than 6 tablets in 24 hours

Children under 12 years ask a doctor

Other information

- do not use if imprinted safety seal under cap is broken or missing

Storage

- store at room temperature 20°– 25°C (68°– 77°F)

Inactive ingredients

croscarmellose sodium, lactose, FD&C red #40 aluminum lake, FD&C yellow #6 aluminum lake,

hypromellose, magnesium stearate, microcrystalline cellulose, silicon dioxide, titanium dioxide.

May contain propylene glycol

Questions

Call 1-888-952-0050 Monday through Friday

Principal Display Panel

Decongestant PE